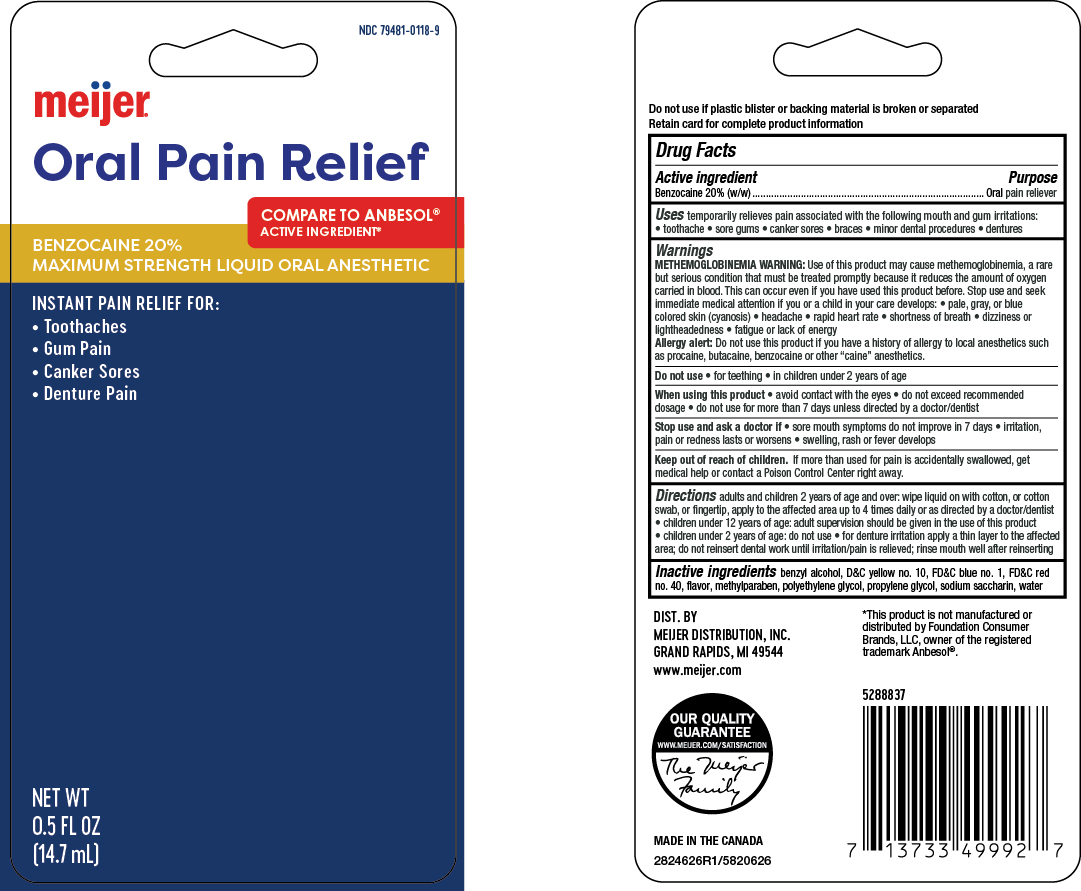 DRUG LABEL: Oral Anesthetic Liquid
NDC: 79481-0118 | Form: LIQUID
Manufacturer: Meijer, Inc.
Category: otc | Type: HUMAN OTC DRUG LABEL
Date: 20250812

ACTIVE INGREDIENTS: BENZOCAINE 20 g/100 g
INACTIVE INGREDIENTS: BENZYL ALCOHOL; WATER; POLYETHYLENE GLYCOL 400; D&C YELLOW NO. 10; FD&C BLUE NO. 1; SACCHARIN SODIUM; PROPYLENE GLYCOL; METHYLPARABEN; FD&C RED NO. 40

5820626 Meijer Oral Anesthetic Liquid

Active Ingredient

Benzocaine 20.0% (w/w)

Purpose

Oral pain reliever

Uses

Temporarily relieves pain associated with the following mouth and gum irritations:

- toothache
- sore gums
- canker sores
- braces
- minor dental procedures
- dentures

Warnings

METHEMOGLOBINEMIA WARNING: Use of this product may cause methemoglobinemia, a rare but serious confition that must be treated promptly because it reduces the amount of oxygen carried in blood. This can occur even if you have used this product before. Stop use and seek immediate medical attention if you or a child in your care develops:

- pale, gray, or blue colored skin (cyanosis)
- headache
- rapid heart rate
- shortness of breath
- dizziness or lightheadedness
- fatigue or lack of energy

Allergy Alert: do not use this product if you have a history of allergy to local anesthetics such as procaine, butacaine, benzocaine or other "caine" anesthetics

Do not use

- for teething
- in children under 2 years of age

When using this product

- avoid contact with eyes
- do not exceed recommended dosage
- do not use for more than 7 days unless directed by a dentist or doctor

Stop use and ask doctor if

- sore mouth symptoms do not improve in 7 days
- irritation, pain or redness persists or worsens
- swelling, rash or fever develops

Directions

Adults and children 2 years of age and older: wipe liquid on with cotton, or cotton swab, or fingertip, apply to the affected area up to 4 times daily or as directed by a doctor/dentist

- children under 12 years of age: adult supervision should be given in the use of this product
- children under 2 years of age: do not use
- for denture irritation apply a thin layer to the affected area; do not reinsert dental work until irritation/pain is relieved; rinse mouth well after reinserting

Inactive ingredients

Benzyl Alcohol, D&C Yellow no. 10, FD&C Blue no. 1, FD&C Red no. 40, Flavor, Methylparaben, Polyethylene Glycol, Propylene Glycol, Sodium Saccharin, Water

Keep out of reach of children. If swallowed, get medical help or contact a Poison Control Center right away.